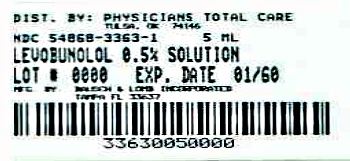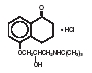 DRUG LABEL: Levobunolol Hydrochloride
NDC: 54868-3363 | Form: SOLUTION/ DROPS
Manufacturer: Physicians Total Care, Inc.
Category: prescription | Type: HUMAN PRESCRIPTION DRUG LABEL
Date: 20120612

ACTIVE INGREDIENTS: LEVOBUNOLOL HYDROCHLORIDE 5 mg/1 mL
INACTIVE INGREDIENTS: BENZALKONIUM CHLORIDE; SODIUM PHOSPHATE, DIBASIC; EDETATE DISODIUM; HYDROCHLORIC ACID; POTASSIUM PHOSPHATE, MONOBASIC; POLYVINYL ALCOHOL; WATER; SODIUM CHLORIDE; SODIUM HYDROXIDE; SODIUM METABISULFITE

Levobunolol Hydrochloride Ophthalmic Solution

Description

Levobunolol Hydrochloride Ophthalmic Solution USP is a noncardioselective beta-adrenoceptor blocking agent for ophthalmic use.

Levobunolol hydrochloride is represented by the following structural formula:

C17H25NO3•HCl

Mol. Wt. 327.85

Chemical Name: (-)-5-[3-(tert-Butylamino)-2-hydroxypropoxy]-3,4-dihydro-1(2H)-naphthalenone hydrochloride.

Each mL of 0.25% and 0.5% contains:

ACTIVE: Levobunolol Hydrochloride 2.5 mg (0.25%) and 5 mg (0.5%); INACTIVES: Polyvinyl Alcohol 1.4%, Sodium Chloride, Dibasic Sodium Phosphate, Edetate Disodium, Sodium Metabisulfite, Monobasic Potassium Phosphate, and Purified Water. Hydrochloric Acid and/or Sodium Hydroxide may be added to adjust pH (5.5 - 7.5); PRESERVATIVE ADDED: Benzalkonium Chloride (0.004%).

Clinical Pharmacology

Levobunolol hydrochloride is greater than 60 times more potent than its dextro isomer in its beta-blocking activity, yet equipotent in its potential for direct myocardial depression. Accordingly, the levo isomer, levobunolol hydrochloride, is used. Levobunolol hydrochloride does not have significant local anesthetic (membrane-stabilizing) or intrinsic sympathomimetic activity.

Beta-adrenergic receptor blockade reduces cardiac output in both healthy subjects and patients with heart disease. In patients with severe impairment of myocardial function, beta-adrenergic receptor blockade may inhibit the stimulatory effect of the sympathetic nervous system necessary to maintain adequate cardiac function.

Beta-adrenergic receptor blockade in the bronchi and bronchioles results in increased airway resistance from unopposed parasympathetic activity. Such an effect in patients with asthma or other bronchospastic conditions is potentially dangerous.

Levobunolol has been shown to be an active agent in lowering elevated as well as normal intraocular pressure (IOP) whether or not accompanied by glaucoma. Elevated IOP presents a major risk factor in glaucomatous field loss. The higher the level of IOP, the greater the likelihood of optic nerve damage and visual field loss.

The onset of action with one drop of levobunolol can be detected within one hour after treatment, with maximum effect seen between 2 and 6 hours.

A significant decrease in IOP can be maintained for up to 24 hours following a single dose.

In two separate, controlled studies (one three month and one up to 12 months duration) levobunolol hydrochloride ophthalmic solution 0.25% b.i.d. controlled the IOP of approximately 64% and 70% of the subjects. The overall mean decrease from baseline was 5.4 mm Hg and 5.1 mm Hg respectively. In an open-label study levobunolol hydrochloride ophthalmic solution 0.25% q.d. controlled the IOP of 72% of the subjects while achieving an overall mean decrease of 5.9 mm Hg.

In controlled clinical studies of approximately two years duration, intraocular pressure was well-controlled in approximately 80% of subjects treated with levobunolol hydrochloride ophthalmic solution 0.5% b.i.d. The mean IOP decrease from baseline was between 6.87 mm Hg and 7.81 mm Hg. No significant effects on pupil size, tear production or corneal sensitivity were observed. Levobunolol hydrochloride at the concentrations tested, when applied topically, decreased heart rate and blood pressure in some patients. The IOP-lowering effect of levobunolol was well maintained over the course of these studies.

In a three month clinical study, a single daily application of levobunolol hydrochloride ophthalmic solution 0.5% controlled the IOP of 72% of subjects achieving an overall mean decrease in IOP of 7.0 mm Hg.

The primary mechanism of the ocular hypotensive action of levobunolol hydrochloride in reducing IOP is most likely a decrease in aqueous humor production. Levobunolol reduces IOP with little or no effect on pupil size or accommodation in contrast to the miosis which cholinergic agents are known to produce. The blurred vision and night blindness often associated with miotics would not be expected and have not been reported with the use of levobunolol. This is particularly important in cataract patients with central lens opacities who would experience decreased visual acuity with pupillary constriction.

Indications and Usage

Levobunolol Hydrochloride Ophthalmic Solution has been shown to be effective in lowering intraocular pressure and may be used in patients with chronic open-angle glaucoma or ocular hypertension.

Contraindications

Levobunolol Hydrochloride Ophthalmic Solution is contraindicated in those individuals with bronchial asthma or with a history of bronchial asthma, or severe chronic obstructive pulmonary disease (see WARNINGS); sinus bradycardia; second and third degree atrioventricular block; overt cardiac failure (see WARNINGS); cardiogenic shock; or hypersensitivity to any component of these products.

Warnings

As with other topically applied ophthalmic drugs, levobunolol may be absorbed systemically. The same adverse reactions found with systemic administration of beta-adrenergic blocking agents may occur with topical administration. For example, severe respiratory reactions and cardiac reactions, including death due to bronchospasm in patients with asthma, and rarely death in association with cardiac failure, have been reported with topical application of beta-adrenergic blocking agents (see CONTRAINDICATIONS).

Cardiac Failure

Sympathetic stimulation may be essential for support of the circulation in individuals with diminished myocardial contractility, and its inhibition by beta-adrenergic receptor blockade may precipitate more severe failure.

In Patients Without a History of Cardiac Failure

Continued depression of the myocardium with beta-blocking agents over a period of time can, in some cases, lead to cardiac failure. At the first sign or symptom of cardiac failure, levobunolol should be discontinued.

Obstructive Pulmonary Disease:

PATIENTS WITH CHRONIC OBSTRUCTIVE PULMONARY DISEASE (e.g. CHRONIC BRONCHITIS, EMPHYSEMA) OF MILD OR MODERATE SEVERITY, BRONCHOSPASTIC DISEASE OR A HISTORY OF BRONCHOSPASTIC DISEASE (OTHER THAN BRONCHIAL ASTHMA OR A HISTORY OF BRONCHIAL ASTHMA, IN WHICH LEVOBUNOLOL IS CONTRAINDICATED, See CONTRAINDICATIONS), SHOULD IN GENERAL NOT RECEIVE BETA BLOCKERS, INCLUDING LEVOBUNOLOL. However, if levobunolol is deemed necessary in such patients, then it should be administered cautiously since it may block bronchodilation produced by endogenous and exogenous catecholamine stimulation of beta2 receptors.

Major Surgery

The necessity or desirability of withdrawal of beta-adrenergic blocking agents prior to major surgery is controversial. Beta-adrenergic receptor blockade impairs the ability of the heart to respond to beta-adrenergic mediated reflex stimuli. This may augment the risk of general anesthesia in surgical procedures. Some patients receiving beta-adrenergic receptor blocking agents have been subject to protracted severe hypotension during anesthesia. Difficulty in restarting and maintaining the heartbeat has also been reported. For these reasons, in patients undergoing elective surgery, gradual withdrawal of beta-adrenergic receptor blocking agents may be appropriate. If necessary during surgery, the effects of beta-adrenergic blocking agents may be reversed by sufficient doses of such agonists as isoproterenol, dopamine, dobutamine or levaterenol (see OVERDOSAGE).

Diabetes Mellitus

Beta-adrenergic blocking agents should be administered with caution in patients subject to spontaneous hypoglycemia or to diabetic patients (especially those with labile diabetes) who are receiving insulin or oral hypoglycemic agents. Beta-adrenergic receptor blocking agents may mask the signs and symptoms of acute hypoglycemia.

Thyrotoxicosis

Beta-adrenergic blocking agents may mask certain clinical signs (e.g. tachycardia) of hyperthyroidism. Patients suspected of developing thyrotoxicosis should be managed carefully to avoid abrupt withdrawal of beta-adrenergic blocking agents, which might precipitate a thyroid storm.

These products contain sodium metabisulfite, a sulfite that may cause allergic-type reactions including anaphylactic symptoms and life-threatening or less severe asthmatic episodes in certain susceptible people. The overall prevalence of sulfite sensitivity in the general population is unknown and probably low. Sulfite sensitivity is seen more frequently in asthmatic than in non-asthmatic people.

Precautions

General

Levobunolol should be used with caution in patients with known hypersensitivity to other beta-adrenoceptor blocking agents. Use with caution in patients with known diminished pulmonary function.

Levobunolol should be used with caution in patients who are receiving a beta-adrenergic blocking agent orally, because of the potential for additive effects on systemic beta-blockade or on intraocular pressure. Patients should not typically use two or more topical ophthalmic beta-adrenergic blocking agents simultaneously.

Because of the potential effects of beta-adrenergic blocking agents on blood pressure and pulse rates, these medications must be used cautiously in patients with cerebrovascular insufficiency. Should signs or symptoms develop that suggest reduced cerebral blood flow while using levobunolol, alternative therapy should be considered.

In patients with angle-closure glaucoma, the immediate objective of treatment is to reopen the angle. This requires, in most cases, constricting the pupil with a miotic. Levobunolol Hydrochloride Ophthalmic Solution has little or no effect on the pupil. When levobunolol is used to reduce elevated intraocular pressure in angle-closure glaucoma, it should be followed with a miotic and not alone.

Muscle Weakness:

Beta-adrenergic blockade has been reported to potentiate muscle weakness consistent with certain myasthenic symptoms (e.g., diplopia, ptosis, and generalized weakness).

Drug interactions

Although levobunolol used alone has little or no effect on pupil size, mydriasis resulting from concomitant therapy with levobunolol and epinephrine may occur.

Close observation of the patient is recommended when a beta-blocker is administered to patients receiving catecholamine-depleting drugs such as reserpine, because of possible additive effects and the production of hypotension and/or marked bradycardia, which may produce vertigo, syncope, or postural hypotension. Patients receiving beta-adrenergic blocking agents along with either oral or intravenous calcium antagonists should be monitored for possible atrioventricular conduction disturbances, left ventricular failure and hypotension. In patients with impaired cardiac function, simultaneous use should be avoided altogether. The concomitant use of betaadrenergic blocking agents with digitalis and calcium antagonists may have additive effects on prolonging atrioventricular conduction time.

Phenothiazine-related compounds and beta-adrenergic blocking agents may have additive hypotensive effects due to the inhibition of each other's metabolism.

Risk of anaphylactic reaction:

While taking beta-blockers, patients with a history of severe anaphylactic reactions to a variety of allergens may be more reactive to repeated challenge, either accidental, diagnostic or therapeutic. Such patients may be unresponsive to the usual doses of epinephrine used to treat allergic reaction.

Animal Studies:

No adverse ocular effects were observed in rabbits administered levobunolol hydrochloride topically in studies lasting one year in concentrations up to 10 times the human dose concentration.

Carcinogenesis, mutagenesis, impairment of fertility

In a lifetime oral study in mice, there were statistically significant (p < 0.05) increases in the incidence of benign leiomyomas in female mice at 200 mg/kg/day (14,000 times the recommended human dose for glaucoma), but not at 12 or 50 mg/kg/day (850 and 3,500 times the human dose). In a two-year oral study of levobunolol hydrochloride in rats, there was a statistically significant (p < 0.05) increase in the incidence of benign hepatomas in male rats administered 12,800 times the recommended human dose for glaucoma. Similar differences were not observed in rats administered oral doses equivalent to 350 times to 2,000 times the recommended human dose for glaucoma.

Levobunolol did not show evidence of mutagenic activity in a battery of microbiological and mammalian in vitro and in vivo assays.

Reproduction and fertility studies in rats showed no adverse effect on male or female fertility at doses up to 1,800 times the recommended human dose for glaucoma.

Pregnancy

Category C:

Fetotoxicity (as evidenced by a greater number of resorption sites) has been observed in rabbits when doses of levobunolol hydrochloride equivalent to 200 and 700 times the recommended dose for the treatment of glaucoma were given. No fetotoxic effects have been observed in similar studies with rats at up to 1,800 times the human dose for glaucoma. Teratogenic studies with levobunolol in rats at doses up to 25 mg/kg/day (1,800 times the recommended human dose for glaucoma) showed no evidence of fetal malformations. There were no adverse effects on post-natal development of offspring. It appears when results from studies using rats and studies with other beta-adrenergic blockers are examined, that the rabbit may be a particularly sensitive species. There are no adequate and well-controlled studies in pregnant women. Levobunolol hydrochloride ophthalmic solution should be used during pregnancy only if the potential benefit justifies the potential risk to the fetus.

Nursing mothers

It is not known whether this drug is excreted in human milk. Systemic beta-blockers and topical timolol maleate are known to be excreted in human milk. Caution should be exercised when Levobunolol hydrochloride ophthalmic solution is administered to a nursing woman.

Pediatric use

Safety and effectiveness in pediatric patients have not been established.

Geriatric use

No overall differences in safety or effectiveness have been observed between elderly and younger patients.

Adverse Reactions

In clinical trials the use of levobunolol hydrochloride has been associated with transient ocular burning and stinging in up to 1 in 3 patients, and with blepharoconjunctivitis in up to 1 in 20 patients. Decreases in heart rate and blood pressure have been reported (see CONTRAINDICATIONS and WARNINGS).

The following adverse effects have been reported rarely with the use of levobunolol: iridocyclitis, headache, transient ataxia, dizziness, lethargy, urticaria and pruritus.

Decreased corneal sensitivity has been noted in a small number of patients. Although levobunolol has minimal membrane-stabilizing activity, there remains a possibility of decreased corneal sensitivity after prolonged use.

The following additional adverse reactions have been reported either with levobunolol or ophthalmic use of other beta-adrenergic receptor blocking agents: BODY AS A WHOLE: Headache, asthenia, chest pain. CARDIOVASCULAR: Bradycardia, arrhythmia, hypotension, syncope, heart block, cerebral vascular accident, cerebral ischemia, congestive heart failure, palpitation, cardiac arrest. DIGESTIVE: Nausea, diarrhea. PSYCHIATRIC: Depression, confusion, increase in signs and symptoms of myasthenia gravis, paresthesia. SKIN: Hypersensitivity, including localized and generalized rash, alopecia, Stevens-Johnson Syndrome. RESPIRATORY: Bronchospasm (predominantly in patients with pre-existing bronchospastic disease), respiratory failure, dyspnea, nasal congestion. UROGENITAL: Impotence. ENDOCRINE: Masked symptoms of hypoglycemia in insulin-dependent diabetics (see WARNINGS). SPECIAL SENSES: Signs and symptoms of keratitis, blepharoptosis, visual disturbances including refractive changes (due to withdrawal of miotic therapy in some cases), diplopia, ptosis.

Other reactions associated with the oral use of non-selective adrenergic receptor blocking agents should be considered potential effects with ophthalmic use of these agents.

Overdosage

No data are available regarding overdosage in humans. Should accidental ocular overdosage occur, flush eye(s) with water or normal saline. If accidentally ingested, efforts to decrease further absorption may be appropriate (gastric lavage).

The most common signs and symptoms to be expected with overdosage with administration of a systemic beta-adrenergic blocking agent are symptomatic bradycardia, hypotension, bronchospasm, and acute cardiac failure. Should these symptoms occur, discontinue levobunolol therapy and initiate appropriate supportive therapy. The following supportive measures should be considered:

1. Symptomatic bradycardia: Use atropine sulfate intravenously in a dosage of 0.25 mg to 2 mg to induce vagal blockade. If bradycardia persists, intravenous isoproterenol hydrochloride should be administered cautiously. In refractory cases the use of a transvenous cardiac pacemaker should be considered.

2. Hypotension: Use sympathomimetic pressor drug therapy, such as dopamine, dobutamine or levarterenol. In refractory cases, the use of glucagon hydrochloride may be useful.

3. Bronchospasm: Use isoproterenol hydrochloride. Additional therapy with aminophylline may be considered.

4. Acute cardiac failure: Conventional therapy with digitalis, diuretics and oxygen should be instituted immediately. In refractory cases the use of intravenous aminophylline is suggested. This may be followed, if necessary, by glucagon hydrochloride which may be useful.

5. Heart block (second or third degree): Use isoproterenol hydrochloride or a transvenous cardiac pacemaker.

Dosage and Administration

The recommended starting dose is one to two drops of levobunolol hydrochloride ophthalmic solution 0.5% in the affected eye(s) once a day. Typical dosing with levobunolol hydrochloride ophthalmic solution 0.25% is one to two drops twice daily. In patients with more severe or uncontrolled glaucoma, levobunolol hydrochloride ophthalmic solution 0.5% can be administered b.i.d. As with any new medication, carefully monitoring of patients is advised.

Dosages above one drop of levobunolol hydrochloride ophthalmic solution 0.5% b.i.d. are not generally more effective. If the patient's IOP is not at a satisfactory level on this regimen, concomitant therapy with dipivefrin and/or epinephrine, and/or pilocarpine and other miotics, and/or systemically administered carbonic anhydrase inhibitors, such as acetazolamide, can be instituted. Patients should not typically use two or more topical ophthalmic beta-adrenergic blocking agents simultaneously.

How Supplied

Levobunolol hydrochloride ophthalmic solution USP, is supplied in a plastic bottle with a controlled drop tip in the following sizes:

0.5% 5 mL bottles - NDC 54868-3363-1

Storage

Store between 15°-30°C (59°-86°F). Protect from light. Replace cap immediately after use.

DO NOT USE IF IMPRINTED NECKBAND IS NOT INTACT

KEEP OUT OF REACH OF CHILDREN

STERILE OPHTHALMIC SOLUTION

Rx only

FOR USE IN THE EYES ONLY

Manufacturing Information

Bausch & Lomb Incorporated

Tampa, Florida 33637 ©Bausch & Lomb Incorporated

9117400 (Folded)

9117500 (Flat)

Additional barcode labeling by:
Physicians Total Care, inc.
Tulsa, Oklahoma 74146

Principal Dipslay Panel

NDC 54868-3363-1

Levobunolol Hydrochloride Ophthmalic Solution USP,
0.5% (Sterile)

Rx only